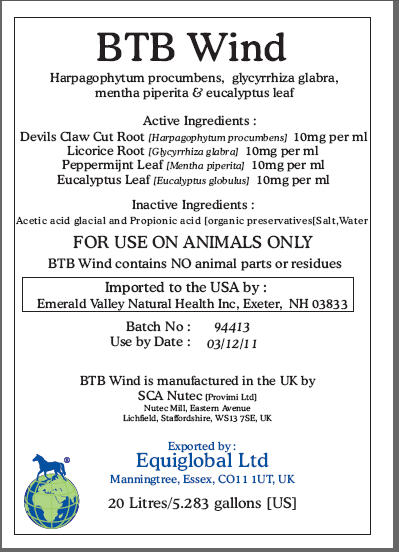 DRUG LABEL: BTB Wind
NDC: 52338-627 | Form: EXTRACT
Manufacturer: SCA NuTec
Category: animal | Type: PRESCRIPTION ANIMAL DRUG LABEL
Date: 20100419

ACTIVE INGREDIENTS: HARPAGOPHYTUM PROCUMBENS ROOT 10 mg/1 mL; GLYCYRRHIZA GLABRA 10 mg/1 mL; PEPPERMINT 10 mg/1 mL; EUCALYPTUS GLOBULUS LEAF 10 mg/1 mL

BTB Wind

Harpagophytum procumbens, glycyrrhiza glabra, mentha piperita & eucalyptus leaf

Active Ingredients:

Devils Claw Cut Root [Harpagophytum procumbens] 10mg per ml
Licorice Root [Glycyrrhiza glabra] 10mg per ml
Peppermijnt Leaf [Mentha piperita] 10mg per ml
Eucalyptus Leaf [Eucalyptus globulus] 10mg per ml

Inactive Ingredients:

Acetic acid glacial and Propionic acid [organic preservatives[Salt,Water

WARNINGS

FOR USE ON ANIMALS ONLY

BTB Wind contains NO animal parts or residues

Imported to the USA by :
Emerald Valley Natural Health Inc, Exeter, NH 03833
Batch No: 94413
Use by Date: 03/12/11
BTB Wind is manufactured in the UK by
SCA Nutec [Provimi Ltd]
Nutec Mill, Eastern Avenue
Lichfield, Staffordshire, WS13 7SE, UK
Exported by :
Equiglobal Ltd
Manningtree, Essex, CO11 1UT, UK
20 Litres/5.283 gallons [US]